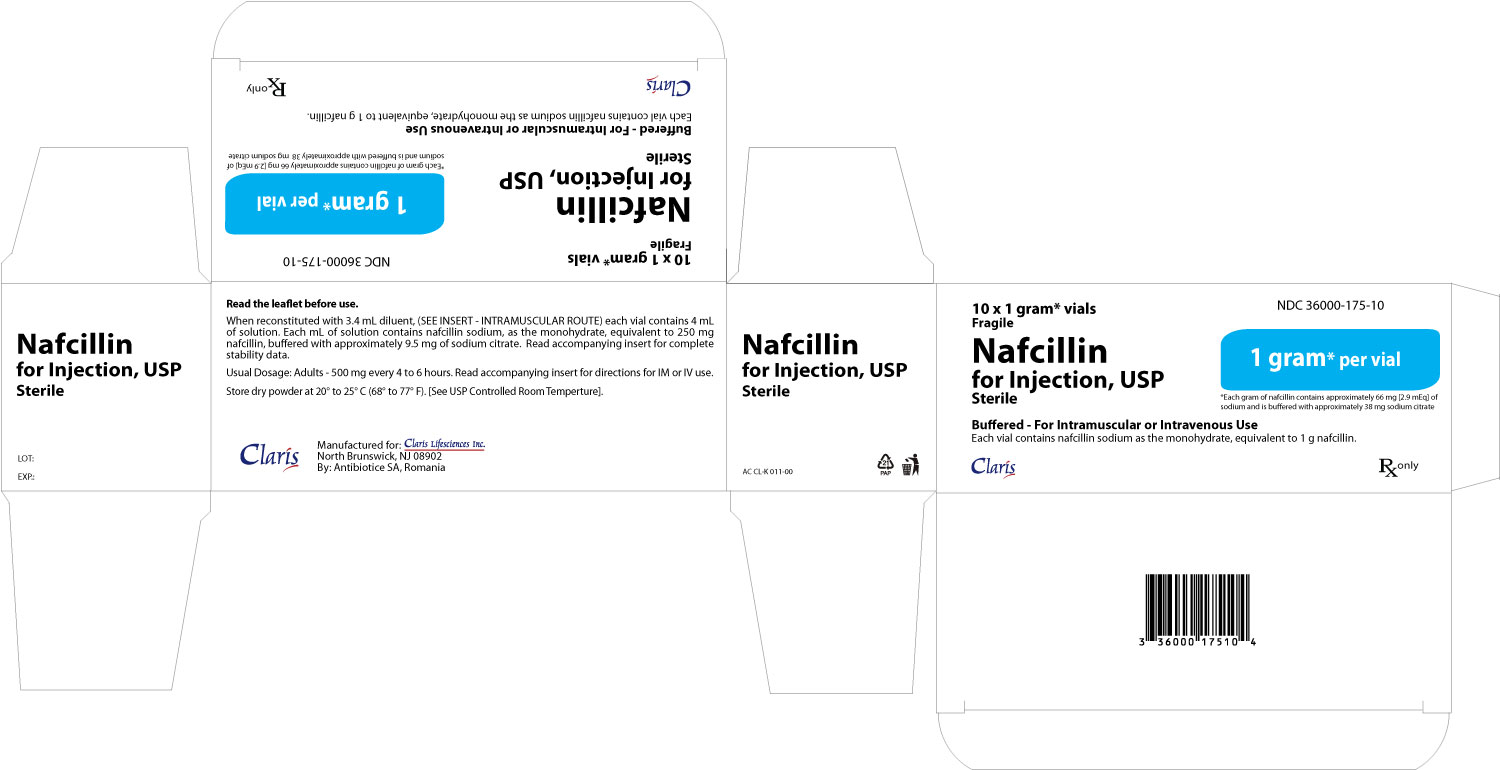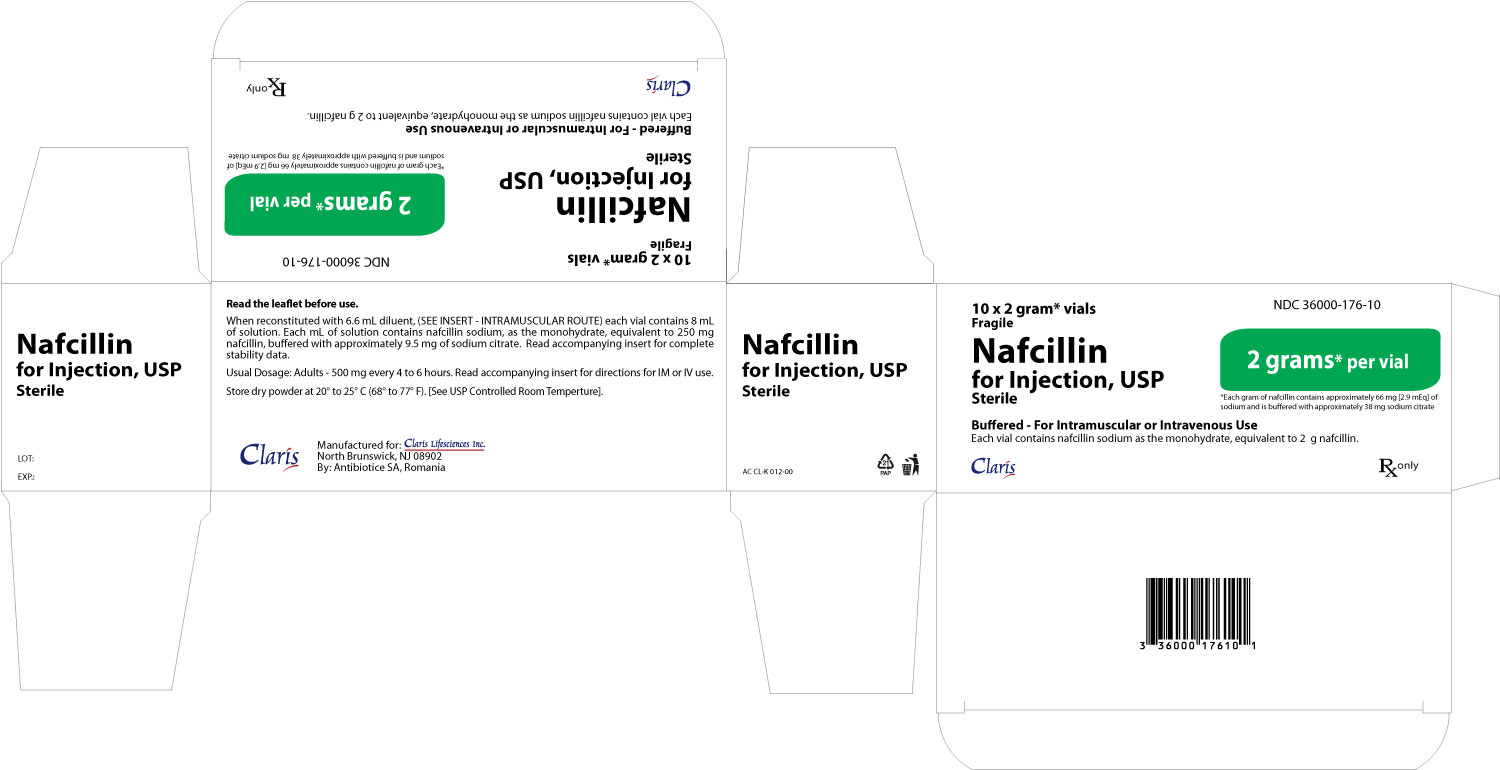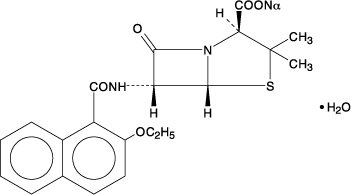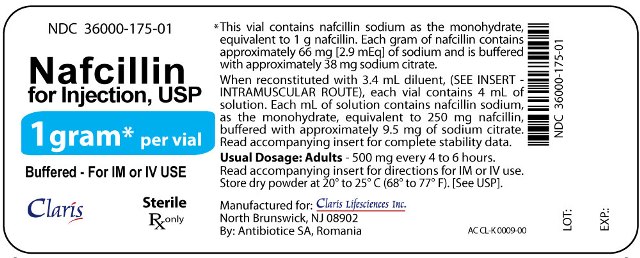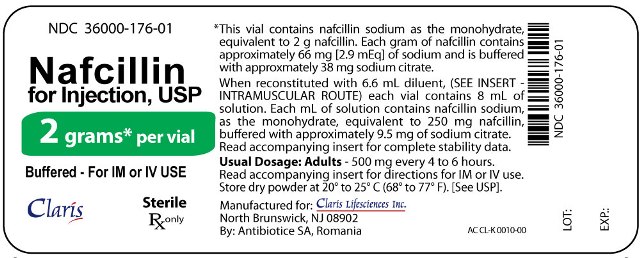 DRUG LABEL: Nafcillin
NDC: 36000-175 | Form: INJECTION
Manufacturer: Claris Lifesciences, Inc.
Category: prescription | Type: HUMAN PRESCRIPTION DRUG LABEL
Date: 20111018

ACTIVE INGREDIENTS: NAFCILLIN SODIUM 1 g/1 1
INACTIVE INGREDIENTS: SODIUM CITRATE

Nafcillin for Injection, USP

For Intramuscular or Intravenous Injection

To reduce the development of drug-resistant bacteria and maintain the effectiveness of Nafcillin for Injection and other antibacterial drugs, Nafcillin for Injection should be used only to treat or prevent infections that are proven or strongly suspected to be caused by bacteria.

DESCRIPTION

Nafcillin for Injection, USP is a sterile semisynthetic penicillin derived from 6-amino-penicillanic acid. It is the sodium salt in a parenteral dosage form. The chemical name of nafcillin sodium is Monosodium (2S, 5R, 6R)-6-(2-ethoxy-1-naphthamido)-3, 3-dimethyl-7-oxo-4-thia-1-azabicyclo[3.2.0]heptane-2-carboxylate monohydrate. It is resistant to inactivation by the enzyme penicillinase (beta-lactamase). The structural formula of nafcillin sodium is as follows:

C21H21N2NaO5S • H2O MW=454.48

Nafcillin for Injection, USP is available as a white to off-white crystalline dry powder for reconstitution. The reconstituted solution is a clear and colorless solution.

Nafcillin for Injection contains nafcillin sodium as the monohydrate equivalent to 1 gram or 2 grams of nafcillin per vial. The sodium content is 66 mg [2.9 mEq] per gram nafcillin. This product is buffered with approximately 38 mg sodium citrate per gram.

CLINICAL PHARMACOLOGY

In a study of five healthy adults administered a single 500 mg dose of nafcillin by intravenous injection over seven minutes, the mean plasma concentration of the drug was approximately 30 mcg/mL at 5 minutes after injection. The mean area under the plasma concentration-versus-time curve (AUC) for nafcillin in this study was 18.06 mcg•h/mL.

The serum half-life of nafcillin administered by the intravenous route ranged from 33 to 61 minutes as measured in three separate studies.

In contrast to the other penicillinase-resistant penicillins, only about 30% of nafcillin is excreted as unchanged drug in the urine of normal volunteers, and most within the first six hours. Nafcillin is primarily eliminated by nonrenal routes, namely hepatic inactivation and excretion in the bile.

Nafcillin binds to serum proteins, mainly albumin. The degree of protein binding reported for nafcillin is 89.9 ± 1.5%. Reported values vary with the method of study and the investigator.

The concurrent administration of probenecid with nafcillin increases and prolongs plasma concentrations of nafcillin. Probenecid significantly reduces the total body clearance of nafcillin with renal clearance being decreased to a greater extent than nonrenal clearance.

The penicillinase-resistant penicillins are widely distributed in various body fluids, including bile, pleural, amniotic and synovial fluids. With normal doses insignificant concentrations are found in the aqueous humor of the eye. High nafcillin CSF levels have been obtained in the presence of inflamed meninges.

Renal failure does not appreciably affect the serum half-life of nafcillin; therefore, no modification of the usual nafcillin dosage is necessary in renal failure with or without hemodialysis. Hemodialysis does not accelerate the rate of clearance of nafcillin from the blood.

A study which assessed the effects of cirrhosis and extrahepatic biliary obstruction in man demonstrated that the plasma clearance of nafcillin was significantly decreased in patients with hepatic dysfunction. In these patients with cirrhosis and extrahepatic obstruction, nafcillin excretion in the urine was significantly increased from about 30 to 50% of the administered dose, suggesting that renal disease superimposed on hepatic disease could further decrease nafcillin clearance.

Microbiology

Penicillinase-resistant penicillins exert a bactericidal action against penicillin-susceptible microorganisms during the state of active multiplication. All penicillins inhibit the biosynthesis of the bacterial cell wall.

The drugs in this class are highly resistant to inactivation by staphylococcal penicillinase and are active against penicillinase-producing strains of Staphylococcus aureus.

The penicillinase-resistant penicillins are active in vitro against a variety of other bacteria.

Susceptibility Tests

Diffusion Techniques

Quantitative methods that require measurement of zone diameters provide reproducible estimates of the susceptibility of bacteria to antimicrobial compounds. One such standardized procedure^1 that has been recommended for use with disks to test the susceptibility of microorganisms to nafcillin uses the 1 µg nafcillin disk. Interpretation involves correlation of the diameter obtained in the disk test with the MIC for nafcillin. Reports from the laboratory providing results of the standard single-disk susceptibility test with a 1 µg nafcillin disk should be interpreted according to the following criteria:

Zone Diameter (mm) | Interpretation
≥ 13 | Susceptible (S)
11-12 | Intermediate (I)
≤ 10 | Resistant (R)

A report of “Susceptible” indicates that the pathogen is likely to be inhibited by usually achievable concentrations of the antimicrobial compound in blood. A report of “Intermediate” indicates that the result should be considered equivocal, and, if the microorganism is not fully susceptible to alternative, clinically feasible drugs, the test should be repeated. This category implies possible clinical applicability in body sites where the drug is physiologically concentrated or in situations where high dosage of drug can be used. This category also provides a buffer zone that prevents small uncontrolled technical factors from causing major discrepancies in interpretation. A report of “Resistant” indicates that usually achievable concentrations of the antimicrobial compound in the blood are unlikely to be inhibitory and that other therapy should be selected.

Measurement of MIC or MBC and achieved antimicrobial compound concentrations may be appropriate to guide therapy in some infections. (See CLINICAL PHARMACOLOGY section for further information on drug concentrations achieved in infected body sites and other pharmacokinetic properties of this antimicrobial drug product.)

Standardized susceptibility test procedures require the use of laboratory control microorganisms. The 1 µg nafcillin disk should provide the following zone diameters in these laboratory test quality control strains:

Microorganism | Zone Diameter (mm)
S. aureus ATCC 25923 | 16-22

Dilution techniques:

Quantitative methods that are used to determine minimum inhibitory concentrations provide reproducible estimates of the susceptibility of bacteria to antimicrobial compounds. One such standardized procedure uses a standardized dilution method^2 (broth, agar, or microdilution) or equivalent with nafcillin powder. The MIC values obtained should be interpreted according to the following criteria:

MIC (μg/mL) | Interpretation
≤ 2 | Susceptible (S)
- | Intermediate (I)
≥ 4 | Resistant (R)

Interpretation should be as stated above for results using diffusion techniques. As with standard diffusion techniques, dilution methods require the use of laboratory control microorganisms. Standard nafcillin powder should provide the following MIC values:

Microorganism | MIC (μg/mL)
S. aureus ATCC 29213 | 0.12-0.5
E. faecalis ATCC 29212 | 2-8

Pharmacokinetics

Intramuscular injections of Nafcillin for Injection 1 gram produced peak serum levels in 0.5 to 1 hour of 7.61 mcg/mL. The degree of protein binding reported has been 89.9 +/-1.5%. With normal doses Nafcillin is found in therapeutic concentrations in the pleural, bile, and amniotic fluids. Insignificant concentrations are found in the cerebrospinal fluid and aqueous humor. Blood concentrations may be tripled by the concurrent use of probenecid. Clinical studies with nafcillin sodium in infants under three days of age and prematures have revealed higher blood levels and slower rates of urinary excretion than in older children and adults. A high concentration of nafcillin sodium is excreted via the bile. About 30% of an intramuscular dose is excreted in the urine.

INDICATIONS AND USAGE

Nafcillin is indicated in the treatment of infections caused by penicillinase-producing staphylococci which have demonstrated susceptibility to the drug. Culture and susceptibility tests should be performed initially to determine the causative organism and its susceptibility to the drug (see CLINICAL PHARMACOLOGY - Susceptibility Tests).

Nafcillin may be used to initiate therapy in suspected cases of resistant staphylococcal infections prior to the availability of susceptibility test results. Nafcillin should not be used in infections caused by organisms susceptible to penicillin G. If the susceptibility tests indicate that the infection is due to an organism other than a resistant Staphylococcus, therapy should not be continued with Nafcillin for Injection, USP.

To reduce the development of drug-resistant bacteria and maintain the effectiveness of Nafcillin for Injection and other antibacterial drugs, Nafcillin for Injection should be used only to treat or prevent infections that are proven or strongly suspected to be caused by susceptible bacteria. When culture and susceptibility information are available, they should be considered in selecting or modifying antibacterial therapy. In the absence of such data, local epidemiology and susceptibility patterns may contribute to the empiric selection of therapy.

CONTRAINDICATIONS

A history of a hypersensitivity (anaphylactic) reaction to any penicillin is a contraindication.

WARNINGS

SERIOUS AND OCCASIONALLY FATAL HYPERSENSITIVITY (ANAPHYLACTIC) REACTIONS HAVE BEEN REPORTED IN PATIENTS ON PENICILLIN THERAPY. THESE REACTIONS ARE MORE LIKELY TO OCCUR IN INDIVIDUALS WITH A HISTORY OF PENICILLIN HYPERSENSITIVITY AND/OR A HISTORY OF SENSITIVITY TO MULTIPLE ALLERGENS. THERE HAVE BEEN REPORTS OF INDIVIDUALS WITH A HISTORY OF PENICILLIN HYPERSENSITIVITY WHO HAVE EXPERIENCED SEVERE REACTIONS WHEN TREATED WITH CEPHALOSPORINS. BEFORE INITIATING THERAPY WITH NAFCILLIN, CAREFUL INQUIRY SHOULD BE MADE CONCERNING PREVIOUS HYPERSENSITIVITY REACTIONS TO PENICILLINS, CEPHALOSPORINS, OR OTHER ALLERGENS. IF AN ALLERGIC REACTION OCCURS, NAFCILLIN SHOULD BE DISCONTINUED AND APPROPRIATE THERAPY INSTITUTED. SERIOUS ANAPHYLACTIC REACTIONS REQUIRE IMMEDIATE EMERGENCY TREATMENT WITH EPINEPHRINE. OXYGEN, INTRAVENOUS STEROIDS, AND AIRWAY MANAGEMENT, INCLUDING INTUBATION, SHOULD ALSO BE ADMINISTERED AS INDICATED.

Clostridium difficile associated diarrhea (CDAD) has been reported with use of nearly all antibacterial agents, including Nafcillin for Injection, and may range in severity from mild diarrhea to fatal colitis. Treatment with antibacterial agents alters the normal flora of the colon leading to overgrowth of C. difficile.

C. difficile produces toxins A and B which contribute to the development of CDAD. Hypertoxin producing strains of C. difficile cause increased morbidity and mortality, as these infections can be refractory to antimicrobial therapy and may require colectomy. CDAD must be considered in all patients who present with diarrhea following antibiotic use. Careful medical history is necessary since CDAD has been reported to occur over two months after the administration of antibacterial agents.

If CDAD is suspected or confirmed, ongoing antibiotic use not directed against C. difficile may need to be discontinued. Appropriate fluid and electrolyte management, protein supplementation, antibiotic treatment of C. difficile, and surgical evaluation should be instituted as clinically indicated.

PRECAUTIONS

General

Nafcillin should generally not be administered to patients with a history of sensitivity to any penicillin.

Penicillin should be used with caution in individuals with histories of significant allergies and/or asthma. Whenever allergic reactions occur, penicillin should be withdrawn unless, in the opinion of the physician, the condition being treated is life-threatening and amenable only to penicillin therapy. The use of antibiotics may result in overgrowth of nonsusceptible organisms. If new infections due to bacteria or fungi occur, the drug should be discontinued and appropriate measures taken.

The liver/biliary tract is the primary route of nafcillin clearance. Caution should be exercised when patients with concomitant hepatic insufficiency and renal dysfunction are treated with nafcillin. Serum levels should be measured and the dosage adjusted appropriately to avoid possible neurotoxic reactions associated with very high concentrations (see DOSAGE AND ADMINISTRATION).

Prescribing Nafcillin for Injection, USP in the absence of a proven or strongly suspected bacterial infection or a prophylactic indication is unlikely to provide benefit to the patient and increases the risk of the development of drug-resistant bacteria.

Information for Patients

Patients should be counseled that antibacterial drugs including Nafcillin for Injection, USP should only be used to treat bacterial infections. They do not treat viral infections (e.g., the common cold). When Nafcillin for Injection is prescribed to treat a bacterial infection, patients should be told that although it is common to feel better early in the course of therapy, the medication should be taken exactly as directed. Skipping doses or not completing the full course of therapy may (1) decrease the effectiveness of the immediate treatment and (2) increase the likelihood that bacteria will develop resistance and will not be treatable by Nafcillin for Injection or other antibacterial drugs in the future.

Diarrhea is a common problem caused by antibiotics which usually ends when the antibiotic is discontinued. Sometimes after starting treatment with antibiotics, patients can develop watery and bloody stools (with or without stomach cramps and fever) even as late as two or more months after having taken the last dose of the antibiotic. If this occurs, patients should contact their physician as soon as possible.

Laboratory Tests

Bacteriologic studies to determine the causative organisms and their susceptibility to nafcillin should be performed (see CLINICAL PHARMACOLOGY: Microbiology). In the treatment of suspected staphylococcal infections, therapy should be changed to another active agent if culture tests fail to demonstrate the presence of staphylococci.

Periodic assessment of organ system function including renal, hepatic, and hematopoietic should be made during prolonged therapy with nafcillin. White blood cell and differential cell counts should be obtained prior to initiation of therapy and periodically during therapy with nafcillin. Periodic urinalysis, blood urea nitrogen, and creatinine determinations should be performed during therapy with nafcillin. SGOT and SGPT values should be obtained periodically during therapy to monitor for possible liver function abnormalities.

Drug Interactions

Tetracycline, a bacteriostatic antibiotic, may antagonize the bactericidal effect of penicillin, and concurrent use of these drugs should be avoided.

Nafcillin in high dosage regimens, i.e., 2 grams every 4 hours, has been reported to decrease the effects of warfarin. When nafcillin and warfarin are used concomitantly, the prothrombin time should be closely monitored and the dose of warfarin adjusted as necessary. This effect may persist for up to 30 days after nafcillin has been discontinued.

Nafcillin when administered concomitantly with cyclosporine has been reported to result in subtherapeutic cyclosporine levels. The nafcillin-cyclosporine interaction was documented in a patient during two separate courses of therapy. When cyclosporine and nafcillin are used concomitantly in organ transplant patients, the cyclosporine levels should be monitored.

Drug/Laboratory Test Interactions

Nafcillin in the urine can cause a false-positive urine reaction for protein when the sulfosalicyclic acid test is used, but not with the dipstick.

Carcinogenesis, Mutagenesis, Impairment of Fertility

No long term animal studies have been conducted with these drugs. Studies on reproduction (nafcillin) in rats and mice reveal no fetal or maternal abnormalities before conception and continuously through weaning (one generation).

Pregnancy

Teratogenic Effects

Pregnancy Category B

Reproduction studies have been performed in the mouse with oral doses up to 20 times the human dose and orally in the rat at doses up to 40 times the human dose and have revealed no evidence of impaired fertility or harm to the rodent fetus due to nafcillin. There are, however, no adequate or well-controlled studies in pregnant women. Because animal reproduction studies are not always predictive of human response, nafcillin should be used during pregnancy only if clearly needed.

Nursing Mothers

Penicillins are excreted in human milk. Caution should be exercised when penicillins are administered to a nursing woman.

Pediatric Use

The liver/biliary tract is the principal route of nafcillin elimination. Because of immature hepatic and renal function in pediatric patients, nafcillin excretion may be impaired, with abnormally high serum levels resulting. Serum levels should be monitored and the dosage adjusted appropriately.^1,2 There are no approved pediatric patient dosage regimens for intravenous nafcillin. Safety and effectiveness in pediatric patients have not been established.

Geriatric Use

Clinical studies of Nafcillin for Injection did not include sufficient numbers of subjects aged 65 and over to determine whether they respond differently from younger subjects. Other reported clinical experience has not identified differences in responses between the elderly and younger patients. In general, dose selection for an elderly patient should be cautious, usually starting at the low end of the dosing range, reflecting the greater frequency of decreased hepatic, renal, or cardiac function, and of concomitant disease or other drug therapy.

Nafcillin for Injection contains 66 mg (2.9 mEq) of sodium per gram. At the usual recommended doses, patients would receive between 198 and 396 mg/day (8.7 and 17.4 mEq) of sodium. The geriatric population may respond with a blunted natriuresis to salt loading. This may be clinically important with regard to such diseases as congestive heart failure.

ADVERSE REACTIONS

Body as a Whole

The reported incidence of allergic reactions to penicillin ranges from 0.7 to 10 percent (see WARNINGS). Sensitization is usually the result of treatment, but some individuals have had immediate reactions to penicillin when first treated. In such cases, it is thought that the patients may have had prior exposure to the drug via trace amounts present in milk or vaccines. Two types of allergic reactions to penicillins are noted clinically, immediate and delayed.

Immediate reactions usually occur within 20 minutes of administration and range in severity from urticaria and pruritus to angioneurotic edema, laryngospasm, bronchospasm, hypotension, vascular collapse, and death. Such immediate anaphylactic reactions are very rare (see WARNINGS) and usually occur after parenteral therapy but have occurred in patients receiving oral therapy. Another type of immediate reaction, an accelerated reaction, may occur between 20 minutes and 48 hours after administration and may include urticaria, pruritus, and fever.

Although laryngeal edema, laryngospasm, and hypotension occasionally occur, fatality is uncommon. Delayed allergic reactions to penicillin therapy usually occur after 48 hours and sometimes as late as 2 to 4 weeks after initiation of therapy. Manifestations of this type of reaction include serum sickness-like symptoms (i.e., fever, malaise, urticaria, myalgia, arthralgia, abdominal pain) and various skin rashes. Nausea, vomiting, diarrhea, stomatitis, black or hairy tongue, and other symptoms of gastrointestinal irritation may occur, especially during oral penicillin therapy.

Local Reactions

Pain, swelling, inflammation, phlebitis, thrombophlebitis, and occasional skin sloughing at the injection site have occurred with intravenous administration of nafcillin (see DOSAGE AND ADMINISTRATION). Severe tissue necrosis with sloughing secondary to subcutaneous extravasation of nafcillin has been reported.

Nervous System Reactions

Neurotoxic reactions similar to those observed with penicillin G could occur with large intravenous or intraventricular doses of nafcillin especially in patients with concomitant hepatic insufficiency and renal dysfunction (see PRECAUTIONS).

Urogenital Reactions

Renal tubular damage and interstitial nephritis have been associated infrequently with the administration of nafcillin. Manifestations of this reaction may include rash, fever, eosinophilia, hematuria, proteinuria, and renal insufficiency.

Gastrointestinal Reactions

Pseudomembranous colitis has been reported with the use of nafcillin. The onset of pseudomembranous colitis symptoms may occur during or after antibiotic treatment (see WARNINGS).

Metabolic Reactions

Agranulocytosis, neutropenia, and bone marrow depression have been associated with the use of nafcillin.

To report SUSPECTED ADVERSE EVENTS, contact FDA at 1-800-FDA-1088 or www.fda.gov.

OVERDOSAGE

Neurotoxic reactions similar to those observed with penicillin G may arise with intravenous doses of nafcillin especially in patients with concomitant hepatic insufficiency and renal dysfunction (see PRECAUTIONS).

In the case of overdosage, discontinue nafcillin, treat symptomatically and institute supportive measures as required. Hemodialysis does not increase the rate of clearance of nafcillin from the blood.

DOSAGE AND ADMINISTRATION

The penicillinase-resistant penicillins are available for oral administration and for intramuscular and intravenous injection. The sodium salts of methicillin, oxacillin and nafcillin may be administered parenterally and the sodium salts of cloxacillin, dicloxacillin, oxacillin and nafcillin are available for oral use.

Nafcillin for Injection is available for intramuscular and intravenous injection. The usual I.V. dosage for adults is 500 mg every 4 hours. For severe infections, 1 g every 4 hours is recommended. Administer slowly over at least 30 to 60 minutes to minimize the risk of vein irritation and extravasation.

RECOMMENDED DOSAGE FOR NAFCILLIN FOR INJECTION, USP
Drug | Adults | Infants and Children; <40 kg (88 lbs) | Other Recommendations
Nafcillin | 500 mg IM every 4 to 6 hours IV every 4 hours | 25 mg/kg IM twice daily | Neonates 10 mg/kg IM twice daily
 | 1 gram IM every 4 hours (severe infections)

Bacteriologic studies to determine the causative organisms and their susceptibility to nafcillin should always be performed. Duration of therapy varies with the type and severity of infection as well as the overall condition of the patient, therefore it should be determined by the clinical and bacteriological response of the patient. In severe staphylococcal infections, therapy with nafcillin should be continued for at least 14 days. Therapy should be continued for at least 48 hours after the patient has become afebrile, asymptomatic, and cultures are negative. The treatment of endocarditis and osteomyelitis may require a longer duration of therapy.

Concurrent administration of the penicillinase-resistant penicillins and probenecid increases and prolongs serum penicillin levels. Probenecid decreases the apparent volume of distribution and slows the rate of excretion by competitively inhibiting renal tubular secretion of penicillin. Nafcillin-probenecid therapy is generally limited to those infections where very high serum levels of nafcillin are necessary.

No dosage alterations are necessary for patients with renal dysfunction, including those on hemodialysis. Hemodialysis does not accelerate nafcillin clearance from the blood.

For patients with hepatic insufficiency and renal failure, measurement of nafcillin serum levels should be performed and dosage adjusted accordingly.

For intramuscular gluteal injections, care should be taken to avoid sciatic nerve injury. With intravenous administration, particularly in elderly patients, care should be taken because of the possibility of thrombophlebitis.

Parenteral drug products should be inspected visually for particulate matter and discoloration prior to administration whenever solution and container permit.

Do not add supplementary medication to Nafcillin for Injection, USP.

Oral preparations of the penicillinase-resistant penicillins should not be used as initial therapy in serious, life-threatening infections (see PRECAUTIONS - General). Oral therapy with the penicillinase-resistant penicillins may be used to follow-up the previous use of a parenteral agent as soon as the clinical condition warrants. For intramuscular gluteal injections, care should be taken to avoid sciatic nerve injury. With intravenous administration, particularly in elderly patients, care should be taken because of the possibility of thrombophlebitis.

DIRECTIONS FOR USE

For Intramuscular Use

Reconstitute with Sterile Water for Injection, USP, 0.9% Sodium Chloride Injection, USP or Bacteriostatic Water for Injection, USP (with benzyl alcohol or parabens); add 3.4 mL to the 1 g vial for 4 mL resulting solution; 6.6 mL to the 2 g vial for 8 mL resulting solution. All reconstituted vials have a concentration of 250 mg per mL.

The clear solution should be administered by deep intragluteal injection immediately after reconstitution.

Reconstituted Stability

Reconstitute with the required amount of Sterile Water for Injection, USP, 0.9% Sodium Chloride Injection, USP or Bacteriostatic Water for Injection, USP (with benzyl alcohol or parabens). The resulting solutions are stable for 3 days at room temperature or 7 days under refrigeration and 90 days frozen.

For Direct Intravenous Use

The required amount of drug should be diluted in 15 to 30 mL of Sterile Water for Injection, USP or Sodium Chloride Injection, USP and injected over a 5- to 10- minute period. This may be accomplished through the tubing of an intravenous infusion if desirable.

For Administration by Intravenous Drip

Reconstitute as directed above (for intravenous use) prior to diluting with intravenous Solution.

Stability Periods for Nafcillin for Injection, USP
Concentration; mg/mL | Sterile; Water; for; Injection | 0.9%; Sodium; Chloride Injection | M/6; Molar; Sodium; Lactate; Solution | 5%; Dextrose; in Water | 5%; Dextrose; in 0.45%; Sodium; Chloride | 10%; Invert; Sugar | Lactated; Ringers; Solution
ROOM TEMPERATURE (25° C)
10-200 | 24 Hrs | 24 Hrs
30 |  |  | 24 Hrs
2-30 |  |  |  | 24 Hrs | 24 Hrs
10-30 |  |  |  |  |  | 24 Hrs | 24 Hrs
REFRIGERATION (4° C)
10-200 | 7 Days | 7 Days
10-30 |  |  | 7 Days | 7 Days | 7 Days | 7 Days | 7 Days
FROZEN (-15° C)
250 | 90 Days | 90 Days
10-250 |  |  | 90 Days | 90 Days | 90 Days | 90 Days | 90 Days

Only those solutions listed above should be used for the intravenous infusion of Nafcillin for Injection, USP. The concentration of the antibiotic should fall within the range specified. The drug concentration and the rate and volume of the infusion should be adjusted so that the total dose of nafcillin is administered before the drug loses its stability in the solution in use.

There is no clinical experience available on the use of this agent in neonates or infants for this route of administration.

This route of administration should be used for relatively short-term therapy (24 to 48 hours) because of the occasional occurrence of thrombophlebitis particularly in elderly patients.

If another agent is used in conjunction with nafcillin therapy, it should not be physically mixed with nafcillin but should be administered separately.

HOW SUPPLIED

Nafcillin for Injection, USP. Nafcillin sodium equivalent to 1 gram or 2 grams nafcillin per vial.

1 gram vial NDC 36000-175-10 packaged in 10s

2 gram vial NDC 36000-176-10 packaged in 10s

STORAGE AND HANDLING

Store dry powder at 20° to 25° C (68° to 77° F). [See USP controlled room temperature].

REFERENCES

1. National Committee for Clinical Laboratory Standards, Performance Standards for Antimicrobial Disk Susceptibility Tests, Seventh Edition. Approved Standard NCCLS Document M2-A7, Vol. 20, No. 1 NCCLS, Wayne, PA, January, 2000.
2. National Committee for Clinical Laboratory Standards, Methods for Dilution Antimicrobial Susceptibility Tests for Bacteria that Grow Aerobically, Fifth Edition. Approved Standard NCCLS Document M7-A5, Vol. 20, No. 2 NCCLS, Wayne, PA, January, 2000.

Rx only

Manufactured for:

Claris Lifesciences Inc.

North Brunswick, NJ 08902

By: Antibiotice SA, Romania

AC CL-K 013-00

June 2011

1 g Label

NDC 36000-175-10

Nafcillin

for Injection,

USP Sterile

1 g*/Vial Rx only

Buffered - for IM or IV use

*Vial contains nafcillin sodium,

as the monohydrate,

equivalent to 1 g nafcillin.

2 g Label

NDC 36000-176-10

Nafcillin

for Injection,

USP Sterile

2 g*/Vial Rx only

Buffered - for IM or IV use

*Vial contains nafcillin sodium,

as the monohydrate,

equivalent to 2 g nafcillin.